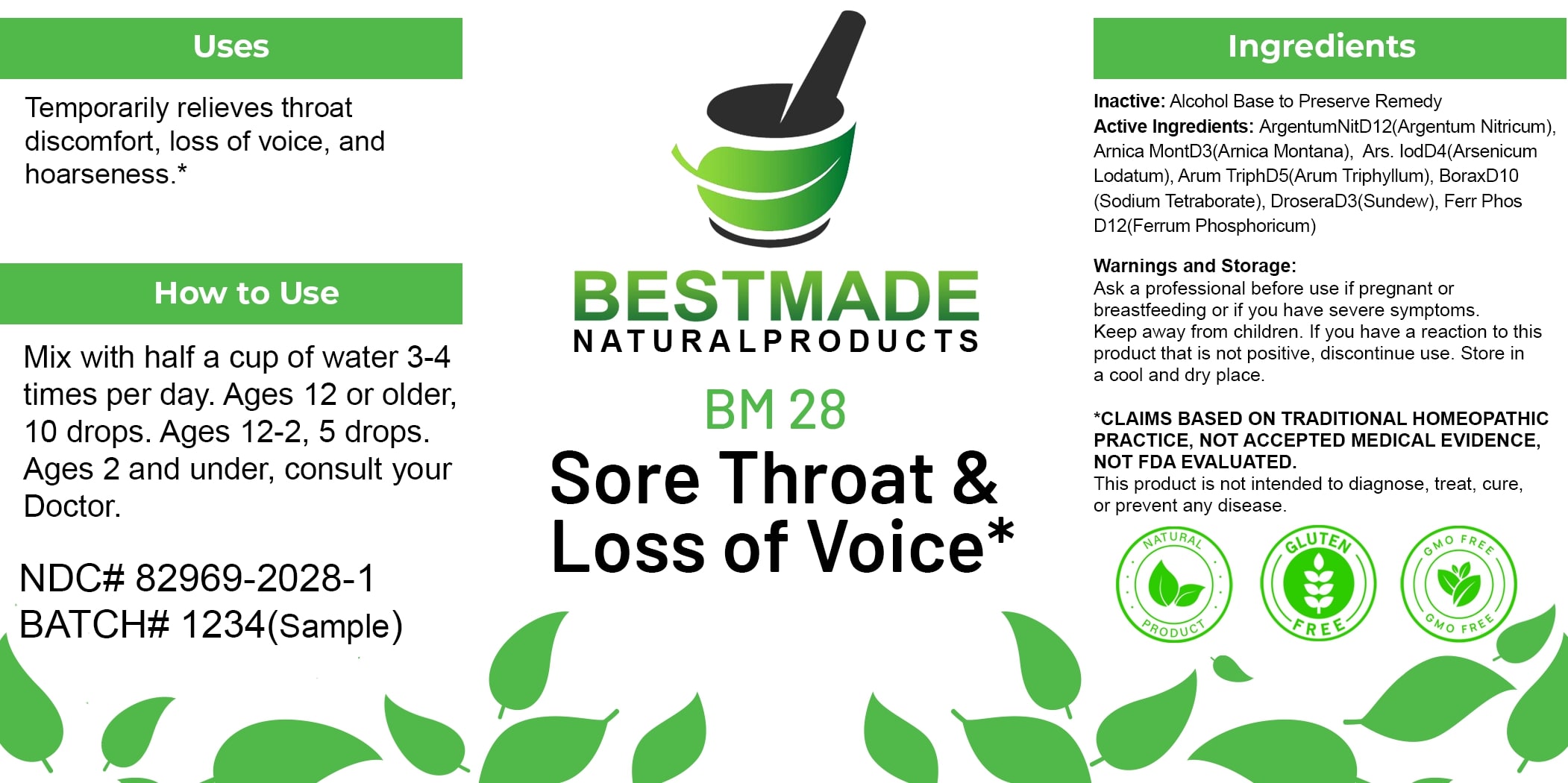 DRUG LABEL: Bestmade Natural Products BM28
NDC: 82969-2028 | Form: LIQUID
Manufacturer: Bestmade Natural Products
Category: homeopathic | Type: HUMAN OTC DRUG LABEL
Date: 20250123

ACTIVE INGREDIENTS: ARISAEMA TRIPHYLLUM ROOT 30 [hp_C]/30 [hp_C]; SILVER NITRATE 30 [hp_C]/30 [hp_C]; SODIUM BORATE 30 [hp_C]/30 [hp_C]; DROSERA ROTUNDIFOLIA 30 [hp_C]/30 [hp_C]; ARNICA MONTANA 30 [hp_C]/30 [hp_C]; ARSENIC TRIIODIDE 30 [hp_C]/30 [hp_C]; FERRIC PYROPHOSPHATE 30 [hp_C]/30 [hp_C]
INACTIVE INGREDIENTS: ALCOHOL 30 [hp_C]/30 [hp_C]

BM28

DOSAGE AND ADMINISTRATION

How to Use

Mix with half a cup of water 3-4 times per day. Ages 12 or older, 10 drops. Ages 12-2, 5 drops. Ages 2 and under, consult your Doctor.

INACTIVE INGREDIENT

Ingredients

Inactive: Alcohol Base to Preserve Remedy

Uses

Temporarily relieves throat discomfort, loss of voice, and hoarseness.*

*CLAIMS BASED ON TRADITIONAL HOMEOPATHIC PRACTICE, NOT ACCEPTED MEDICAL EVIDENCE. NOT FDA EVALUATED.

This product is not intended to diagnose, treat, cure, or prevent any disease.

Uses

Temporarily relieves throat discomfort, loss of voice, and hoarseness.*

*CLAIMS BASED ON TRADITIONAL HOMEOPATHIC PRACTICE, NOT ACCEPTED MEDICAL EVIDENCE. NOT FDA EVALUATED.

This product is not intended to diagnose, treat, cure, or prevent any disease.

ACTIVE INGREDIENT

Active Ingredients: Argentum Nitricum D12 (Argentum Nitricum), Arnica Mont D3 (Arnica Montana), Ars. Iod D4 (Arsenicum Iodatum), Arum Triph D5 (Arum Triphyllum), Borax D10 (Sodium Tetraborate), Drosera D3 (Sundew), Ferr Phos D12 (Ferrum Phosphoricum)

KEEP OUT OF REACH OF CHILDREN

Warnings and Storage:

Ask a professional before use if pregnant or breastfeeding or if you have severe symptoms. Keep away from children. If you have a reaction to this product that is not positive, discontinue use. Store in a cool and dry place.

Warnings and Storage:

Ask a professional before use if pregnant or breastfeeding or if you have severe symptoms. Keep away from children. If you have a reaction to this product that is not positive, discontinue use. Store in a cool and dry place.

*CLAIMS BASED ON TRADITIONAL HOMEOPATHIC PRACTICE, NOT ACCEPTED MEDICAL EVIDENCE. NOT FDA EVALUATED.

This product is not intended to diagnose, treat, cure, or prevent any disease.

Entire package label